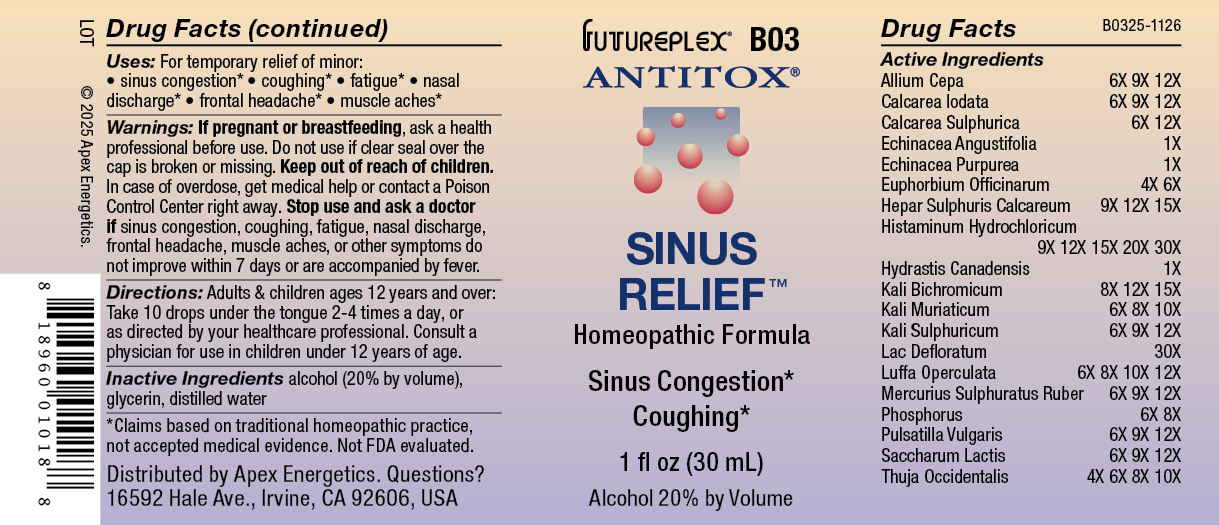 DRUG LABEL: B03
NDC: 63479-0203 | Form: SOLUTION/ DROPS
Manufacturer: Apex Energetics Inc.
Category: homeopathic | Type: HUMAN OTC DRUG LABEL
Date: 20251231

ACTIVE INGREDIENTS: LACTOSE, UNSPECIFIED FORM 12 [hp_X]/1 mL; THUJA OCCIDENTALIS LEAFY TWIG 10 [hp_X]/1 mL; POTASSIUM SULFATE 12 [hp_X]/1 mL; GOLDENSEAL 1 [hp_X]/1 mL; POTASSIUM DICHROMATE 15 [hp_X]/1 mL; POTASSIUM CHLORIDE 10 [hp_X]/1 mL; PULSATILLA VULGARIS 12 [hp_X]/1 mL; PHOSPHORUS 8 [hp_X]/1 mL; SKIM MILK 30 [hp_X]/1 mL; CALCIUM IODIDE 12 [hp_X]/1 mL; ECHINACEA ANGUSTIFOLIA 1 [hp_X]/1 mL; ECHINACEA PURPUREA 1 [hp_X]/1 mL; EUPHORBIA RESINIFERA RESIN 6 [hp_X]/1 mL; CALCIUM SULFIDE 15 [hp_X]/1 mL; HISTAMINE DIHYDROCHLORIDE 30 [hp_X]/1 mL; MERCURIC SULFIDE 12 [hp_X]/1 mL; ONION 12 [hp_X]/1 mL; CALCIUM SULFATE ANHYDROUS 12 [hp_X]/1 mL; LUFFA OPERCULATA FRUIT 12 [hp_X]/1 mL
INACTIVE INGREDIENTS: GLYCERIN; WATER; ALCOHOL

B03

Active Ingredients
Allium Cepa | 6X 9X 12X
Calcarea Iodata | 6X 9X 12X
Calcarea Sulphurica | 6X 12X
Echinacea Angustifolia | 1X
Echinacea Purpurea | 1X
Euphorbium Officinarum | 4X 6X
Hepar Sulphuris Calcareum | 9X 12X 15X
Histaminum Hydrochloricum | 9X 12X 15X 20X 30X
Hydrastis Canadensis | 1X
Kali Bichromicum | 8X 12X 15X
Kali Muriaticum | 6X 8X 10X
Kali Sulphuricum | 6X 9X 12X
Lac Defloratum | 30X
Luffa Operculata | 6X 8X 10X 12X
Mercurius Sulphuratus Ruber | 6X 9X 12X
Phosphorus | 6X 8X
Pulsatilla Vulgaris | 6X 9X 12X
Saccharum Lactis | 6X 9X 12X
Thuja Occidentalis | 4X 6X 8X 10X

INDICATIONS AND USAGE

Uses:

For temporary relief of minor:

sinus congestion*

coughing*

fatigue*

nasal discharge*

frontal headache*

muscle aches*

*Claims based on traditional homeopathic practice, not accepted medical evidence. Not FDA evaluated.

Warnings:

PREGNANCY OR BREAST FEEDING

If pregnant or breastfeeding, ask a health professional before use.

Do not use if clear seal over the cap is broken or missing.

Keep out of reach of children. In case of overdose, get medical help or contact a Poison Control Center right away.

Stop use and ask a doctor if sinus congestion, coughing, fatigue, nasal discharge, frontal headache, muscle aches, or other symptoms do not improve within 7 days or are accompanied by fever.

Directions:

Adults & children ages 12 years and over: Take 10 drops under the tongue 2-4 times a day, or as directed by your healthcare professional. Consult a physician for use in children under 12 years of age.

Inactive Ingredients

alcohol (20% by volume), glycerin, distilled water

Distributed by Apex Energetics. Questions?

16592 Hale Ave., Irvine, CA 92606, USA

PACKAGE LABEL

FUTUREPLEX® B03

ANTITOX®

SINUS RELIEF™

Homeopathic Formula

Sinus Congestion*

Coughing*

1 fl oz (30 mL)

Alcohol 20% by Volume